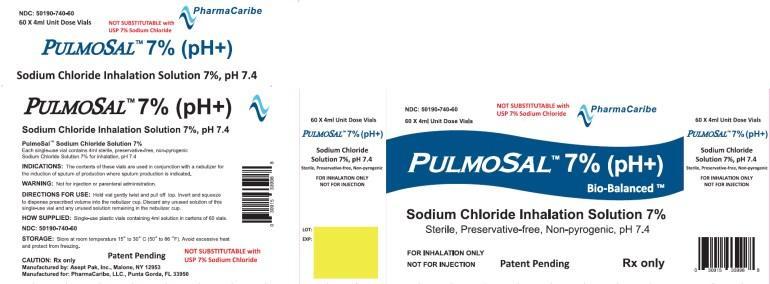 DRUG LABEL: Pulmosal
NDC: 50190-740
Manufacturer: PharmaCaribe
Category: other | Type: MEDICAL DEVICE
Date: 20131120

ACTIVE INGREDIENTS: SODIUM CHLORIDE 280 mg/4 mL

Pulmosal 7% (pH+)

DESCRIPTION

Pulmosal 7% (pH+) 4 mL
Sodium Chloride Inhalation Solution 7%,
Sterile, Preservative-free, Non-pyrogenic, pH 7.4

Each Single-use vial contains 4ml sterile, preservative-free, non-pyrogenic Sodium Chloride Solution 7% for inhalation, pH 7.4
FOR INHALATION ONLY

NOT FOR INJECTION.

Patent Pending
RX Only

60 x 4 mL Unit-Dose Vial

NOT SUBSTITUTABLE with USP 7% Sodium Chloride

INDICATIONS AND USAGE

The contents of these vials are used in conjunction with a nebulizer for the induction of sputum production where sputum production is indicated.

INSTRUCTIONS FOR USE SECTION

Hold vial gently twist and pull off top. Invert and squeeze to dispense prescribed volume into the nebulizer cup. Discard any unused solution of this single-use vial and any unused solution remaining in the nebulizer cup.

How Supplied

Single-use plastic vials containing 4ml solution in cartons of 60 vials.
NDC:50190-740-60

WARNINGS

Not for injection or parenteral administration.

STORAGE

Store at room temperature 15° to 30° C (50° to 86°F). Avoid excessive heat and protect from freezing.

Pulmosal 7% (pH+) 4 mL

PRODUCT CODE 50190-740-60

Rx Only

Manufactured by: Asept Pak, Inc. , Malone, NY 12953

Manufactured For: PharmaCaribe, LLC , Punta Gorda, FL 33950